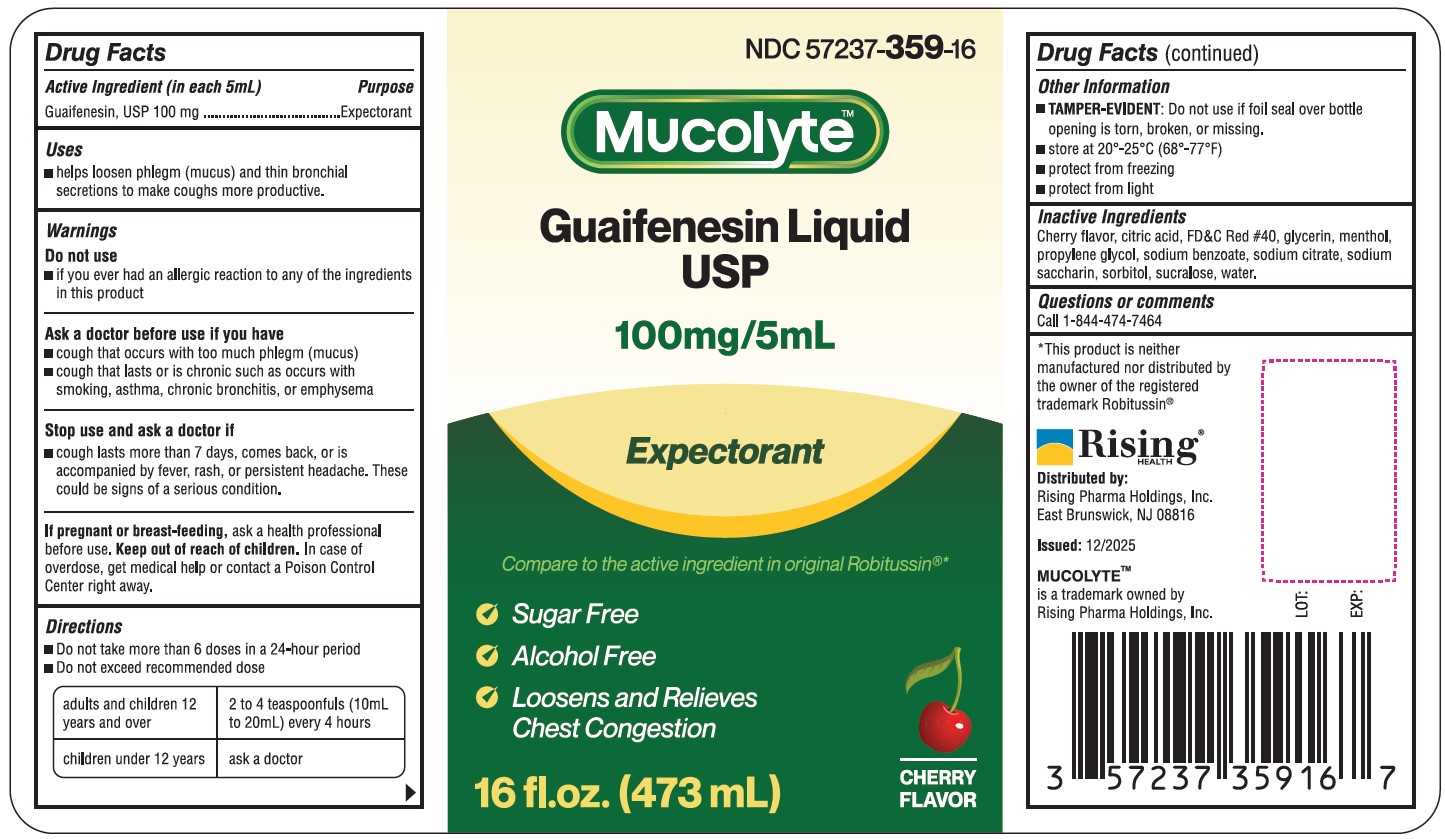 DRUG LABEL: Mucolyte
NDC: 57237-359 | Form: LIQUID
Manufacturer: Rising Pharma Holdings, Inc.
Category: otc | Type: HUMAN OTC DRUG LABEL
Date: 20251208

ACTIVE INGREDIENTS: GUAIFENESIN 100 mg/5 mL
INACTIVE INGREDIENTS: CITRIC ACID; FD&C RED NO. 40; GLYCERIN; MENTHOL; PROPYLENE GLYCOL; SODIUM BENZOATE; SODIUM CITRATE; SODIUM SACCHARIN; SORBITOL; SUCRALOSE; WATER

Mucolyte
Guaifenesin Liquid USP

Drug Facts

Active Ingredient (in each 5mL)

Guaifenesin, USP 100 mg

Purpose

Expectorant

Uses

- helps loosen phlegm (mucus) and thin bronchial secretions to make coughs more productive.

Warnings

Do not use

- if you ever had an allergic reaction to any of the ingredients in this product

Ask a doctor before use if you have

- cough that occurs with too much phlegm (mucus)
- cough that lasts or is chronic such as occurs with smoking, asthma, chronic bronchitis, or emphysema

Stop use and ask a doctor if

- cough lasts more than 7 days, comes back, or is accompanied by fever, rash, or persistent headache. These could be signs of a serious condition.

PREGNANCY OR BREAST FEEDING

If pregnant or breast-feeding, ask a health professional before use.

Keep out of reach of children. In case of overdose, get medical help or contact a Poison Control Center right away.

Directions

- Do not take more than 6 doses in a 24-hour period
- Do not exceed recommended dose

adults and children 12 years and over | 2 to 4 teaspoonfuls (10mL to 20mL) every 4 hours
children under 12 years | ask a doctor

Other Information

- TAMPER-EVIDENT: Do not use if foil seal over bottle opening is torn, broken, or missing.
- store at 20°-25°C (68°-77°F)
- protect from freezing
- protect from light

Inactive Ingredients

Cherry flavor, citric acid, FD&C Red #40, glycerin, menthol, propylene glycol, sodium benzoate, sodium citrate, sodium saccharin, sorbitol, sucralose, water.

Questions or comments

Call 1-844-474-7464

OTHER SAFETY INFORMATION

*This product is neither manufactured nor distributed by the owner of the registered trademark Robitussin®

MUCOLYTETM is a trademark owned by Rising Pharma Holdings, Inc.

Distributed by:
Rising Pharma Holdings, Inc.
East Brunswick, NJ 08816